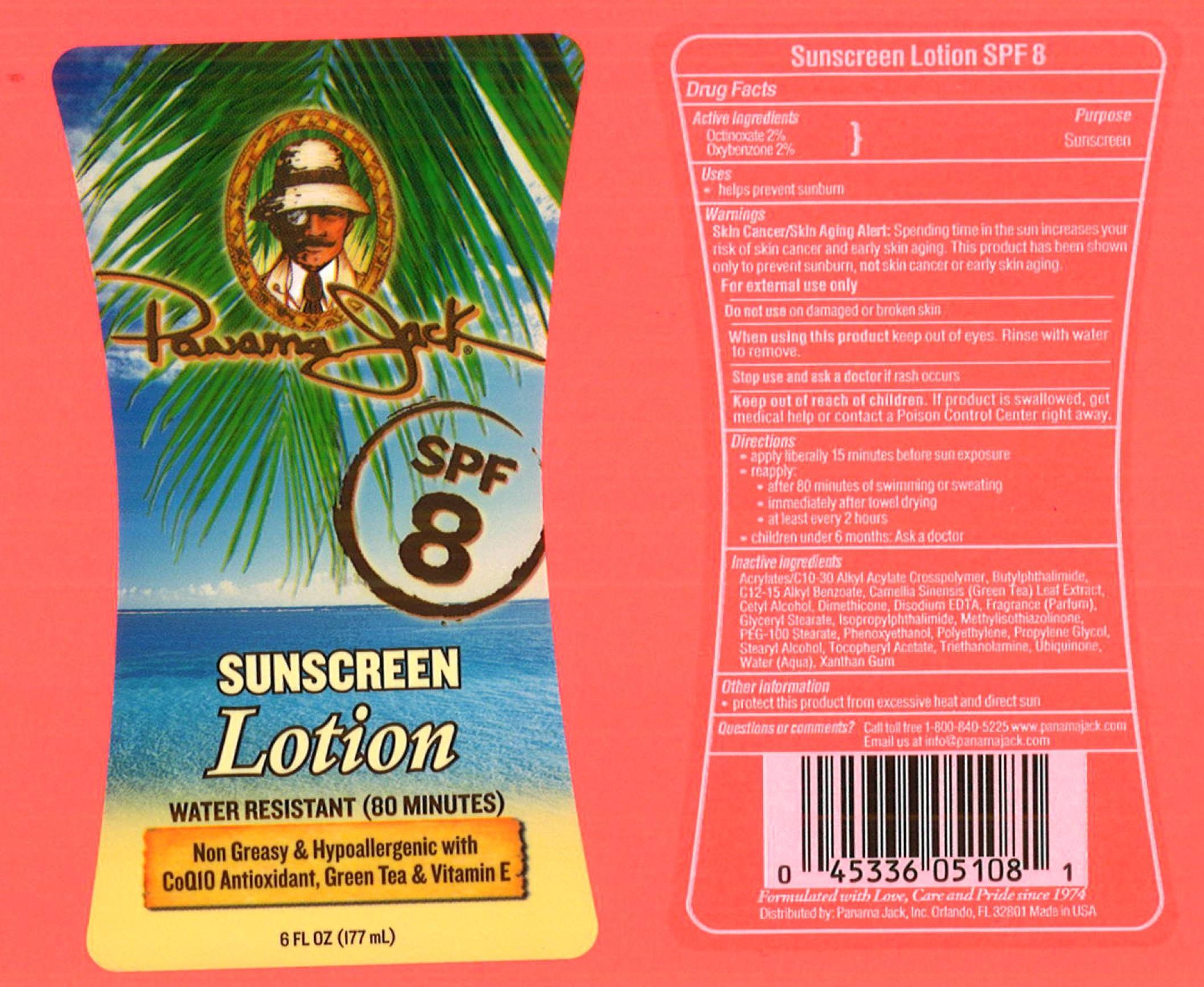 DRUG LABEL: Panama Jack
NDC: 58443-0051 | Form: LOTION
Manufacturer: Prime Enterprises, Inc.
Category: otc | Type: HUMAN OTC DRUG LABEL
Date: 20200117

ACTIVE INGREDIENTS: OCTINOXATE 19.5 mg/1 mL; OXYBENZONE 19.5 mg/1 mL
INACTIVE INGREDIENTS: CARBOMER COPOLYMER TYPE A (ALLYL PENTAERYTHRITOL CROSSLINKED); 3-BUTYLPHTHALIDE; ISOPROPYLPHTHALIMIDE; ALKYL (C12-15) BENZOATE; CETYL ALCOHOL; DIMETHICONE; EDETATE DISODIUM; GLYCERYL MONOSTEARATE; PEG-100 STEARATE; PHENOXYETHANOL; HIGH DENSITY POLYETHYLENE; PROPYLENE GLYCOL; GREEN TEA LEAF; STEARYL ALCOHOL; .ALPHA.-TOCOPHEROL ACETATE; TROLAMINE; UBIDECARENONE; METHYLISOTHIAZOLINONE; XANTHAN GUM

Active ingredients

Octinoxate 2 %, and Oxybenzone 2 %

Purpose

Sunscreen

Uses

- helps prevent sunburn

Warnings

Skin Cancer/Skin Aging Alert: Spending time in the sun increases your risk of skin cancer and early skin aging. This product has been shown only to prevent sunburn, not skin cancer or early skin aging.

OTHER SAFETY INFORMATION

For external use only

Do not use on damaged or broken skin.

When using this product keep out of eyes. Rinse with water to remove.

Stop use and ask a doctor if rash occurs.

Keep out of reach of children. If product is swallowed, get medical help or contact a Poison Control Center right away.

Directions

- apply liberally 15 minutes before sun exposure
- reapply
  - after 80 minutes of swimming or sweating
  - immediately after towel drying
  - at least every 2 hours
- children under 6 months: Ask a doctor

Inactive Ingredients

Acrylates/C10-30 Alkyl Acrylate Crosspolymer, Acrylates/C12-22 Alkyl Methacrylate Copolymer, Allantoin, Aloe Barbadensis Leaf Juice, Butylphthalimide, C12-15 Alkyl Benzoate, Caramel, Carrageenan, Citric Acid, Dimethicone, Disodium EDTA, Fragrance, Hydroxypropyl Methylcellulose, Isopropylphthalimide, Methylisothiazolinone, Methylparaben, Oleth 10, Propylene Glycol, Propylparaben, Soluble Collagen, Sorbitan Oleate, Tocopheryl Acetate, Triethanolamine, Trimethylsiloxysilicate, Water

Other information

- protect this product from excesive heat and direct sun

Questions or Comments?

Call toll free 1-800-840-5225 www.panamajack.com

PRINCIPAL DISPLAY PANEL - 177 mL Bottle Label

Panama Jack

SPF 8

SUNSCREEN

Lotion

WATER RESISTANT (80 MINUTES)

Non Greasy and Hypoallergenic with

CoQIO Anioxidan, Green Tea & Vitamin E

6 FL OZ (177 mL)